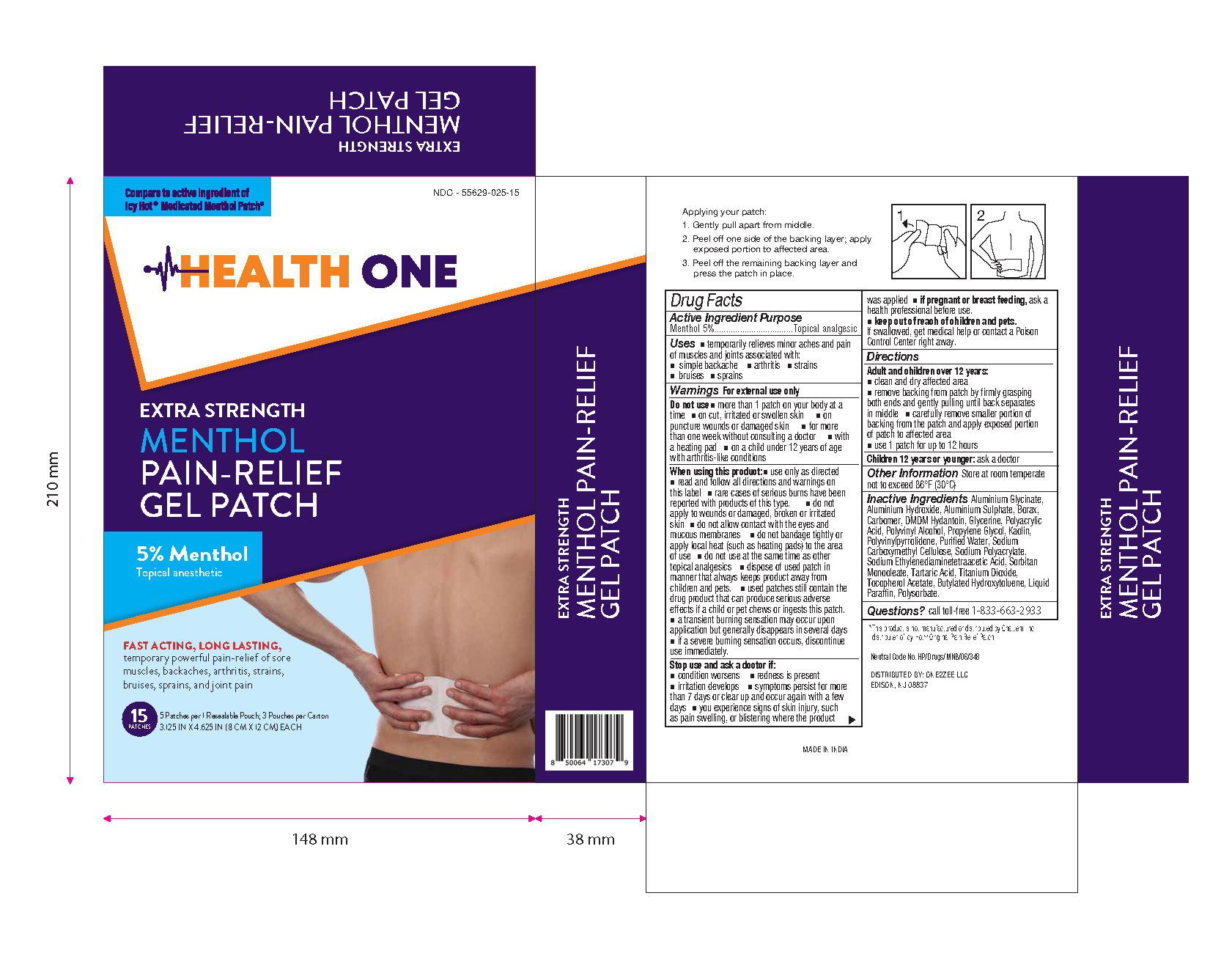 DRUG LABEL: Menthol Pain Relief Gel Patch
NDC: 55629-025 | Form: PATCH
Manufacturer: ONE2ZEE LIMITED LIABILITY COMPANY
Category: otc | Type: HUMAN OTC DRUG LABEL
Date: 20250304

ACTIVE INGREDIENTS: MENTHOL 50 mg/1 1
INACTIVE INGREDIENTS: ALPHA-TOCOPHEROL; ALUMINUM GLYCINATE; ALUMINUM HYDROXIDE; ALUMINUM SULFATE; CARBOMER 934; SODIUM BORATE; SILICON DIOXIDE; DMDM HYDANTOIN; GLYCERIN; KAOLIN; POLYACRYLIC ACID (250000 MW); POLYVINYL ALCOHOL (100000 MW); POVIDONE K27; PROPYLENE GLYCOL; WATER; CARBOXYMETHYLCELLULOSE SODIUM; MAGNESIUM DISODIUM EDTA; SODIUM POLYACRYLATE (2500000 MW); SORBITOL MONOOLEATE; TARTARIC ACID; TITANIUM DIOXIDE; PARAFFIN

Menthol Pain Relief Gel Patch

Active Ingredient

Menthol 5%

Purpose

Topical Anesthetic

Use

Temporarily relieves minor aches and pain of muscles and joints accociated with, simple backache, arthritis, strains, bruises and sprains

Warnings

For external use only

Do not use:

- more than 1 patch on your body at a time
- on cut, irritated or swollen skin
- on puncture wounds or damaged skin
- for more than one week without consulting a doctor
- with heating pad
- on a child under 12 yeas of age with arthritis-like conditions

When using this product:

- use only as directed.
- read and follow all directions and warnings on this label
- rare cases of serious burns have been reported with products of this type.
- do not apply to wounds or damaged, broken or irritated skin
- do not allow contact with eyes and mucous membranes
- do not bandage tightly or apply local heat (such as heating pads) to the area of use
- do not use at the same time as other topical analgesics
- dispose of used patch in manner that always keeps product away from children and pets
- used patches still contain the drug product that can produce serious adverse effects if a child or pet chews or ingests this patch
- a transient burning sensation may occur upon application but generally disappears in several days
- if a severe burning sensation occurs, discontinue use immediately.
- discontinue use at least 1 hour before a bath or shower.
- do not use immediately after a bath or shower.

Stop use and ask a doctor if:

condition worsens

redness is present over the affected area

excess skin irritation occurs

symptoms persist for more than 7 days or clear up and occur again within a few days

you experience signs of skin injury such as pain, swelling, or blistering where the product was applied

PREGNANCY OR BREAST FEEDING

if pregnanat or breast feeding, ask a health professional before use.

keep out of reach of children and pets

if swallowed, get medical help or contact a Poison Control Center right away

Directions:

Adult and children over 12years:

- Clean and dry affected area
- remove backing from patch by firmly grasping both ends and gently pulling until back separates in middle
- carefully remove smaller portion of backing from the patch and apply exposed portion of patch to affected area
- do not wear a patch for more than 8 hours
- apply affected area no more than 3 times daily
- children 12 years or younger: ask a doctor

Other Information:

Store at room temperature 20-25^0C (68-77^0F)

Questions? call toll-free 1-844-912-4012

Inactive Ingredients:

Alpha Tocopherol, Aluminum Sulphate, Borax, Carbomer, Colloidal Silicon Dioxide, DMDM Hydantoin, Glycerin, Kaolin, Polyacrylic Acid, Polyvinyl Alcohol, Polyvinylpyrrolidone , Propylene Glycol, Purified Water, Sodium Carboxymethyl Cellulose, Sodium Ethylenediaminetetraacetic Acid, Sodium Polyacrylate, Sorbitol, Sorbitol Monooleate , Tartaric Acid & Titanium Dioxide, Paraffin